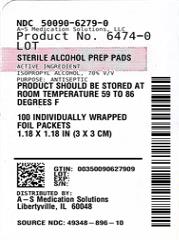 DRUG LABEL: Isopropyl Alcohol
NDC: 50090-6279 | Form: SWAB
Manufacturer: A-S Medication Solutions
Category: otc | Type: HUMAN OTC DRUG LABEL
Date: 20231031

ACTIVE INGREDIENTS: ISOPROPYL ALCOHOL 0.7 mL/1 1
INACTIVE INGREDIENTS: WATER

Isopropyl Alcohol

Drug Facts

Active ingredient

Isopropyl Alcohol, 70% v/v

Purpose

Antiseptic

INDICATIONS AND USAGE

Use for preparation of the skin prior to injection

Warnings

For external use only

- Flammable, keep away from fire or flame

- Do not use: with electrocautery or in eyes

- Stop use: if redness or irritation develops, if condition continues for more than 72 hours consult a physician.

KEEP OUT OF REACH OF CHILDREN

- Keep out of reach from Children: If swallowed, get medical attention or call Poison Control immediately.

Directions

Apply alcohol as needed to clean intended area.

Discard after single use.

Inactive Ingredients

30% purified water.

Other Information

this product should be stored at room temperature: 59° - 86°F(15° - 30°C)

HOW SUPPLIED

Product: 50090-6279

NDC: 50090-6279-0 1 SWAB in a PACKET / 100 in a BOX